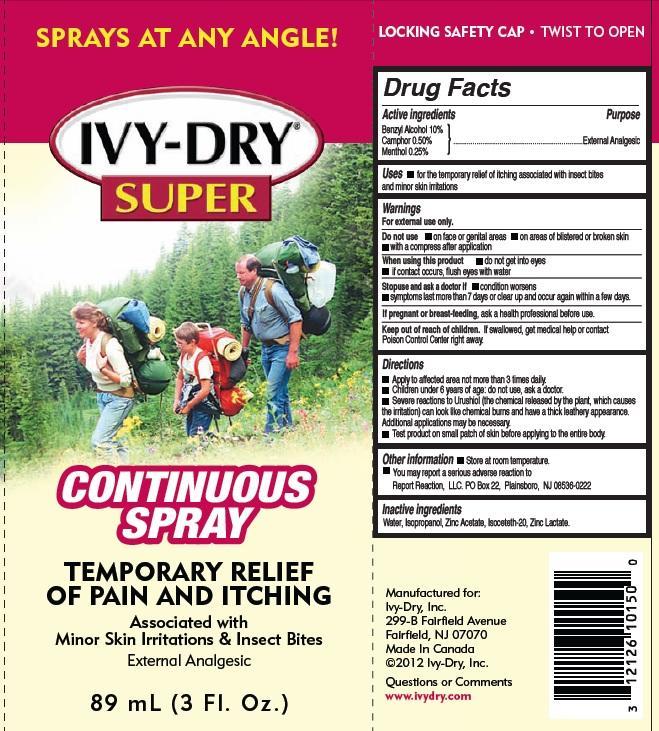 DRUG LABEL: Ivy-Dry Super
NDC: 49546-105 | Form: SPRAY
Manufacturer: Ivy-Dry, Inc.
Category: otc | Type: HUMAN OTC DRUG LABEL
Date: 20171227

ACTIVE INGREDIENTS: BENZYL ALCOHOL 100 mg/1 mL; CAMPHOR (SYNTHETIC) 5 mg/1 mL; MENTHOL 2.5 mg/1 mL
INACTIVE INGREDIENTS: WATER; ISOPROPYL ALCOHOL; ZINC ACETATE; ISOCETETH-20; ZINC LACTATE

Ivy-Dry Super

Active Ingredients

Benzyl Alcohol 10%

Camphor 0.5%

Menthol 0.25%

Purpose

External Analgesic

Uses

- for the temporary relief of itching associated with insect bites and minor skin irritations

WARNINGS

For external use only.

Do not use

- on face or genital areas
- on areas of blistered or broken skin
- with a compress after application

When using this product

- do not get into eyes
- if contact occurs, flush eyes with water

Stop use and ask a doctor if

- condition worsens
- symptoms last more than 7 days or clear up and occur again within a few days.

If pregnant or breast-feeding,

ask a doctor before use.

Keep out of reach of children.

If swallowed, get medical help or contact Poison Control Center right away.

Directions

- Apply to affected area not more than 3 times daily.
- Children under 6 years of age: do not use, ask a doctor.
- Severe reactions to Urushiol (the chemical released by the plant, which causes the irritation) can look like chemical burns and have a thick leathery appearance. Additional applications may be necessary.
- Test product on small patch of skin before applying to the entire body.

Other information

Store at room temperature

You may report a serious adverse reaction to Report Reaction, LLC PO Box 22 Plainsboro, NJ 08536-0222

Inactive Information

Water, Isopropanol, Zinc Acetate, Isoceteth-20, Zinc Lactate.

Package Labeling

Sprays at any angle!

Ivy-Dry Super

Continuous Spray

TEMPORARY RELIEF OF PAIN AND ITCHING

External Analgesic

Manufactured for:
Ivy-Dry, Inc.
299-B Fairfield Avenue
Fairfield, NJ 07070
Made In Canada
©2012 Ivy-Dry, Inc.
Questions or Comments
www.ivydry.com